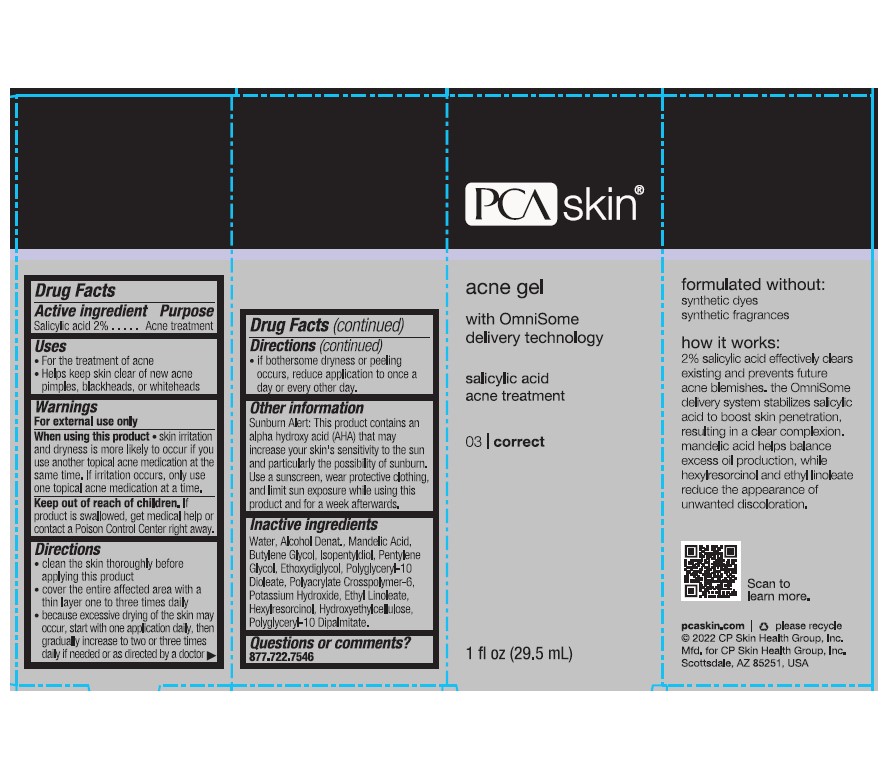 DRUG LABEL: PCA Gel
NDC: 68726-445 | Form: GEL
Manufacturer: CP Skin Health Group, Inc
Category: otc | Type: HUMAN OTC DRUG LABEL
Date: 20241203

ACTIVE INGREDIENTS: SALICYLIC ACID 2 g/100 mL
INACTIVE INGREDIENTS: ALCOHOL; BUTYLENE GLYCOL; POWDERED CELLULOSE; DENATONIUM BENZOATE; DIETHYLENE GLYCOL MONOETHYL ETHER; ETHYL LINOLEATE; HEXYLRESORCINOL; ISOPENTYLDIOL; MANDELIC ACID; PENTYLENE GLYCOL; AMMONIUM ACRYLOYLDIMETHYLTAURATE, DIMETHYLACRYLAMIDE, LAURYL METHACRYLATE AND LAURETH-4 METHACRYLATE COPOLYMER, TRIMETHYLOLPROPANE TRIACRYLATE CROSSLINKED (45000 MPA.S); POLYGLYCERYL-10 OLEATE; POLYGLYCERYL-10 DIPALMITATE; POTASSIUM HYDROXIDE; SODIUM HYDROXIDE; TERT-BUTYL ALCOHOL; WATER

PCA SKIN Acne Gel Advanced Treatment

Active Ingredients

Salicylic Acid 2%

Purpose

Acne Treatment

Uses

- For the treatment of acne
- Helps keep skin clear of new acne pimples, blackheads or whiteheads

Warnings

For external use only

When using this product

- skin irritation and dryness is more likely to occur if you use another topical acne medication at the same time. If irritation occurs, only use one topical medication at a time.

Keep out of reach of children.

If product is swallowed, get medical help or contact a Poison Control Center right away

Directions

- Clean the skin thoroughly before applying this product
- Cover the entire affected area with a thin layer one to three times daily
- because excessive drying of the skin may occur, start with one application daily, then gradually increase to two or three times daily if needed or as directed by a doctor
- if bothersome dryness or peeling occurs, reduce application to once a day or every other day.

Inactive Ingredients

Alcohol, Butylene Glycol, Cellulose, Denatonium Benzoate, Ethoxydiglycol, Ethyl Linoleate, Hexylresorcinol, Hydroxyethylcellulose, Isopentyldiol, Mandelic Acid, Pentylene Glycol, Polyacrylate Crosspolymer-6, Polyglyceryl-10 Dioleate, Polyglyceryl-10 Dipalmitate, Potassium Hydroxide, Sodium Acetate, t-Butyl Alcohol, Water